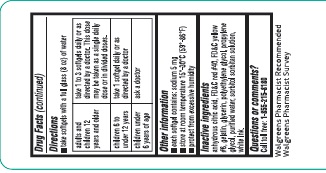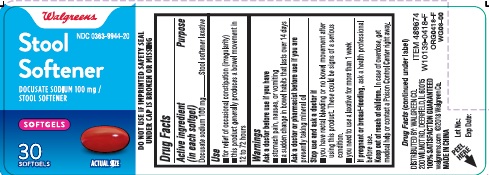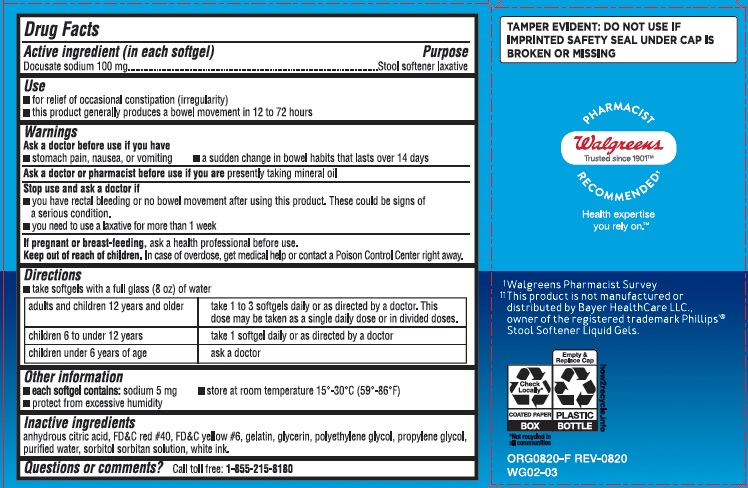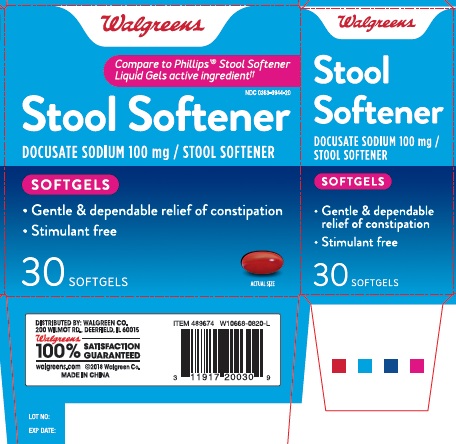 DRUG LABEL: STOOL SOFTENER
NDC: 0363-9944 | Form: CAPSULE, LIQUID FILLED
Manufacturer: Walgreen Co.
Category: otc | Type: HUMAN OTC DRUG LABEL
Date: 20241121

ACTIVE INGREDIENTS: DOCUSATE SODIUM 100 mg/1 1
INACTIVE INGREDIENTS: ANHYDROUS CITRIC ACID; FD&C RED NO. 40; FD&C YELLOW NO. 6; GELATIN; GLYCERIN; POLYETHYLENE GLYCOL, UNSPECIFIED; PROPYLENE GLYCOL; WATER; SORBITOL; SORBITAN

Stool Softener

Drug Facts

Active ingredient (in each softgel)

Docusate sodium 100 mg

Purpose

Stool softener laxative

Uses

- for relief of occasional constipation (irregularity)
- this product generally produces a bowel movement in 12 to 72 hours

Warnings

Ask a doctor before use if you have

- stomach pain, nausea, or vomiting
- a sudden change in bowel habits that lasts over 14 days

Ask a doctor or pharmacist before use if you are presently taking mineral oil

Stop use and ask a doctor if

- you have rectal bleeding or no bowel movement after using this product. These could be signs of a serious condition.
- you need to use a laxative for more than 1 week

PREGNANCY OR BREAST FEEDING

If pregnant or breast-feeding,ask a health professional before use

Keep out of reach of children. In case of overdose, get medical help or contact a Poison Control Center right away.

Directions

take softgels with a full glass (8oz) of water

adults and children 12 years and older | take 1 to 3 softgels daily or as directed by a doctor. This dose may be taken as a single daily dose or in divided doses.
children 6 to under 12 years | take 1 softgel daily or as directed by a doctor
children under 6 years | ask a doctor

Other information

- each softgel contains: sodium 5 mg
- store at room temperature 15°-30°C (59°-86°F)
- protect from excessive humidity

Inactive ingredients

anhydrous citric acid, FD&C red # 40, FD&C yellow #6, gelatin, glycerin, polyethylene glycol, propylene glycol, purified water, sorbitol sorbitan solution and white edible ink

Questions or comments?

Call toll free: 1-855-215-8180

PRINCIPAL DISPLAY PANEL - Carton

Stool Softener

DOCUSATE SODIUM 100 mg 30 SOFTGELS

Compare to Phillips' Stool Softener Liquid Gels active ingredient

NDC 0363-9944-20

PRINCIPAL DISPLAY PANEL - Bottle

Stool Softener

DOCUSATE SODIUM 100 mg 30 SOFTGELS

Compare to Phillips' Stool Softener Liquid Gels active ingredient

NDC 0363-9944-20